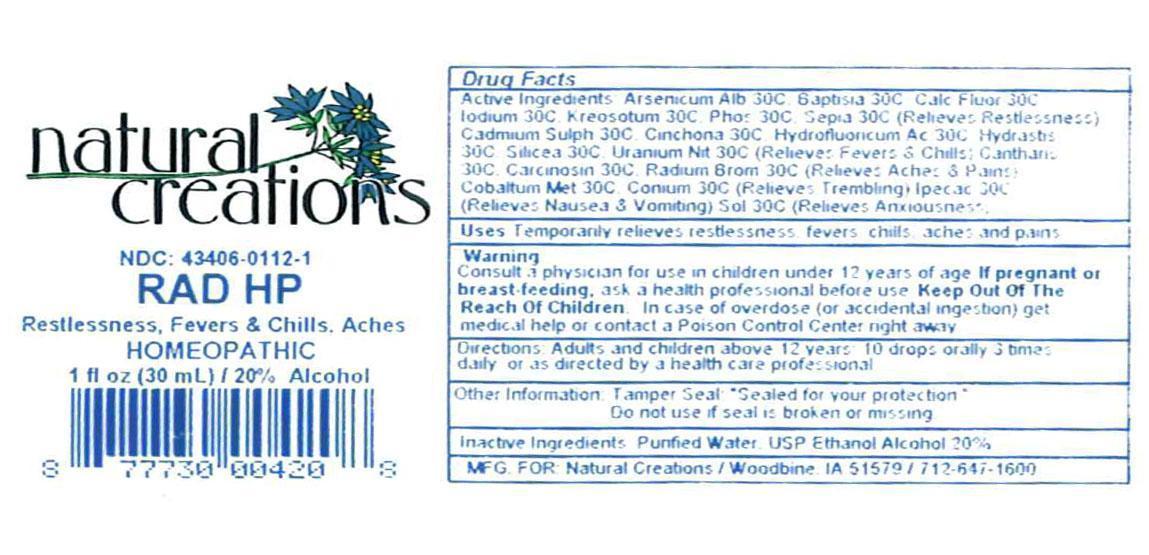 DRUG LABEL: RAD HP
NDC: 43406-0112 | Form: LIQUID
Manufacturer: Natural Creations, Inc.
Category: homeopathic | Type: HUMAN OTC DRUG LABEL
Date: 20130102

ACTIVE INGREDIENTS: ARSENIC TRIOXIDE 30 [hp_C]/1 mL; BAPTISIA TINCTORIA ROOT 30 [hp_C]/1 mL; CADMIUM SULFIDE 30 [hp_C]/1 mL; CALCIUM FLUORIDE 30 [hp_C]/1 mL; LYTTA VESICATORIA 30 [hp_C]/1 mL; HUMAN BREAST TUMOR CELL 30 [hp_C]/1 mL; CINCHONA OFFICINALIS BARK 30 [hp_C]/1 mL; COBALT 30 [hp_C]/1 mL; CONIUM MACULATUM FLOWERING TOP 30 [hp_C]/1 mL; HYDROFLUORIC ACID 30 [hp_C]/1 mL; GOLDENSEAL 30 [hp_C]/1 mL; IODINE 30 [hp_C]/1 mL; IPECAC 30 [hp_C]/1 mL; WOOD CREOSOTE 30 [hp_C]/1 mL; PHOSPHORUS 30 [hp_C]/1 mL; RADIUM BROMIDE 30 [hp_C]/1 mL; SEPIA OFFICINALIS JUICE 30 [hp_C]/1 mL; SILICON DIOXIDE 30 [hp_C]/1 mL; URANYL NITRATE HEXAHYDRATE 30 [hp_C]/1 mL
INACTIVE INGREDIENTS: WATER; ALCOHOL

RAD HP

ACTIVE INGREDIENT

Active Ingredients: Arsenicum Album 30C, Baptisia Tinctoria 30C, Cadmium Sulphate 30C, Calcarea Fluorica 30C, Cantharis Vesicatoria 30C, Carcinosinum 30C, China Officinalis 30C, Cobalt Metal 30C, Conium Maculatum 30C, Fluoricum Acidum 30C, Hydrastis Canadensis 30C, Iodum Purum 30C, Ipecacuanha 30C, Kreosotum 30C, Phosphorus 30C, Radium Bromatum 30C, Sepia Succus 30C, Silica Terra 30C, Sol 30C, Uranium Nitricum 30C

INDICATIONS AND USAGE

USES: Temporarily relieves restlessness, fevers & chills, aches & pains.

WARNING:

Consult a physician for us in children under 12 years of age. IF PREGNANT OR BREAST-FEEDING, ask a health care professional before use. KEEP OUT OF THE REACH OF CHILDREN. In case of overdose (or accidental ingestion) get medical help or contact a Poison Control Center right away.

DOSAGE AND ADMINISTRATION

DIRECTIONS: Adults and children above 12 years: 10 drops orally 3 times daily, or as directed by a health care professional.

OTHER INFORMATION: Tamper Seal: "Sealed for your protection."

Do not use if seal is broken or missing.

INACTIVE INGREDIENTS: Purified Water, USP Ethanol Alocohol 20%

QUESTIONS AND COMMENTS?

MFG FOR: Natural Creations / Woodbine, IA / 51579 712.647.1600

LOT:

PURPOSE

USES: Temporarily relieves restlessness, fevers & chills, aches & pains.

KEEP OUT OF REACH OF CHILDREN

KEEP OUT OF THE REACH OF CHILDREN. In case of overdose (or accidental ingestion) get medical help or contact a Poison Control Center.

PACKAGE LABEL

NDC: 43406-0112-1

RAD HP

Restlessness * Fevers & Chills * Aches

HOMEOPATHIC

1 fl oz (30 mL) / 20% Alcohol

UPC: 877730004208